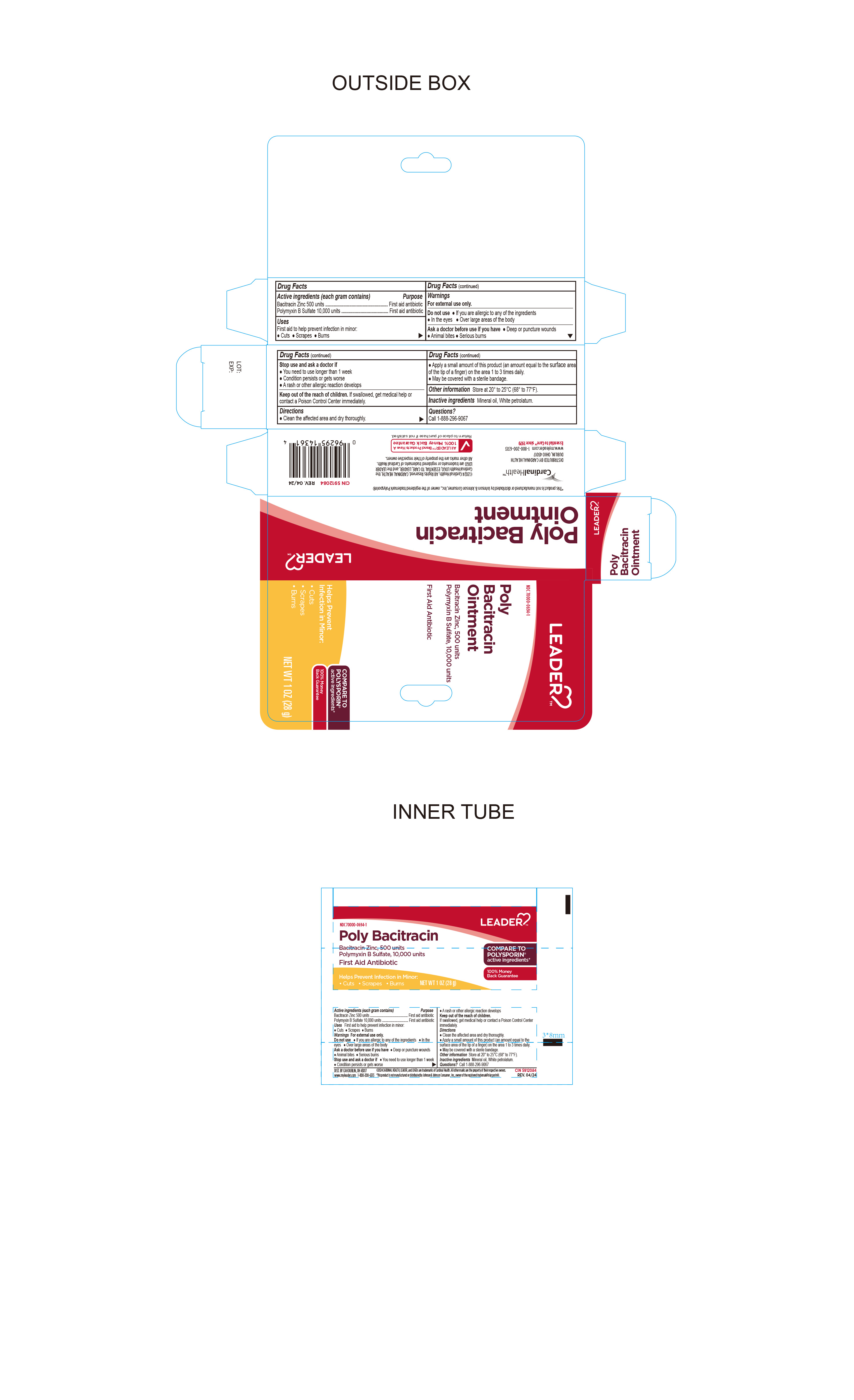 DRUG LABEL: Leader Poly Bacitracin
NDC: 70000-0694 | Form: OINTMENT
Manufacturer: Cardinal Health 110 dba LEADER
Category: otc | Type: HUMAN OTC DRUG LABEL
Date: 20240829

ACTIVE INGREDIENTS: BACITRACIN ZINC 500 [USP'U]/1 g; POLYMYXIN B SULFATE 10000 [USP'U]/1 g
INACTIVE INGREDIENTS: MINERAL OIL; WHITE PETROLATUM

LEADER Poly Bacitracin Ointment

Active Ingredient

Bacitracin Zinc 500 Units per gram

Purpose

First Aid Antibiotic

Acrive Ingredient

Polymixin B Sulfate 10,000 Units Per gram

Purpose

First Aid Antibiotic

Uses

First Aid to help prevent infection in minor

- cuts
- scrapes
- burns

Warnings

For External Use Only.

Do Not Use

- in eyes
- over large areas of the body
- if you are allergic to any of the ingredients

Ask Doctor before Use if you have

deep puncture wounds.

animal bites

serious burns.

Stop Use and Ask Doctor if

- The condition persists or gets worse
- You need to use longer than 1 week.
- A rash or other allergic reaction develops

Directions

- Clean the affected area and dry thoroughly
- Apply a small amount of this product (an amount equal to the surface area of the tip of a finger) on the area 1 to 3 times daily
- May be covered with a sterile bandage

Inactive Ingredients

mineral oil, white petrolatum

Questions

Call 1-888-296-9067

Keep out of reach of children

If swallowed, get medical help or contact a Poison Control Center immediately.

Other Information

Store Between 20°C to 25°C (68° to 77°F)

Distributed By:

Cardinal Health

Dublin, Ohio 43017

www.myleader.com

1-800-200-6313

Essential to Care™ Since 1979

©2024 Cardinal Health. All rights reserved. CARDINAL HEALTH, the Cardinal Health LOGO, ESSENTIAL TO CARE, LEADER, and the leader LOGO are trademarks or registered trademarks of Cardinal Health. All other marks are he property of their respective owners.